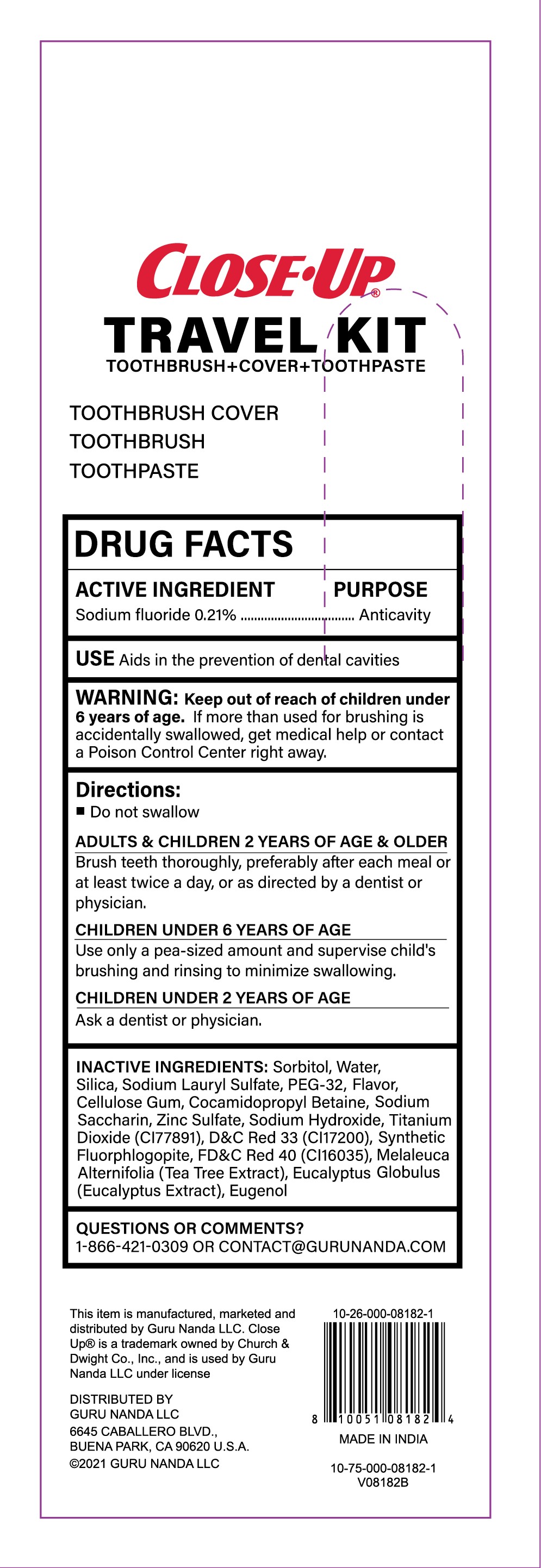 DRUG LABEL: CLOSE UP TRAVEL
NDC: 72025-004 | Form: PASTE, DENTIFRICE
Manufacturer: JHS SVENDGAARD LABORATORIES LIMITED
Category: otc | Type: HUMAN OTC DRUG LABEL
Date: 20220810

ACTIVE INGREDIENTS: SODIUM FLUORIDE 0.21 g/100 g
INACTIVE INGREDIENTS: WATER; SORBITOL; SODIUM LAURYL SULFATE; ALPHA CELLULOSE; SODIUM SILICATE; TITANIUM DIOXIDE; SACCHARIN SODIUM; PEG-32 LAURATE; COCAMIDOPROPYL BETAINE; ZINC SULFATE; SODIUM HYDROXIDE; D&C RED NO. 33; FD&C RED NO. 40; MELALEUCA ALTERNIFOLIA WHOLE; EUCALYPTUS GLOBULUS WHOLE; EUGENOL

72025-004

Active Ingredient

Sodium Fluoride 0.21%

Purpose:

Anticavity

Uses:

Aids in the prevention of dental cavities

Warnings:

If more than used for brushing is accidentally swallowed, get medical help or contact a Poison Control Center right away.

Keep out of reach of children under 6 years of age

Directions:

- Do not swallow.

Adults and children 2 years and older:
Brush teeth thoroughly, preferably after each meal or at least twice a day, or as directed by a dentist or physician.
Children under 6 Years of Age
Use only a pea-sized amount and supervise children's brushing and rinsing to minimize swallowing.

Children under 2 years of age:
Ask a dentist or physician

Inactive Ingredients:

Sorbitor, Water, Silica, Sodium Lauryl Suphate, PEG-32, Titanium Dioxide, Flavor, Cellulose Gum, Cocamidopropyl Betaine, Sodium Saccharin, Zinc Sulfate, Sodium Hydroxide, D&C Red 33, FD&C Red 40, Synthetic Fluorphlogopite, Melaleuca Alternifolia (Tea Tree Extract), Eucalyptus Globulus (Eucalyptus Extract), Eugenol